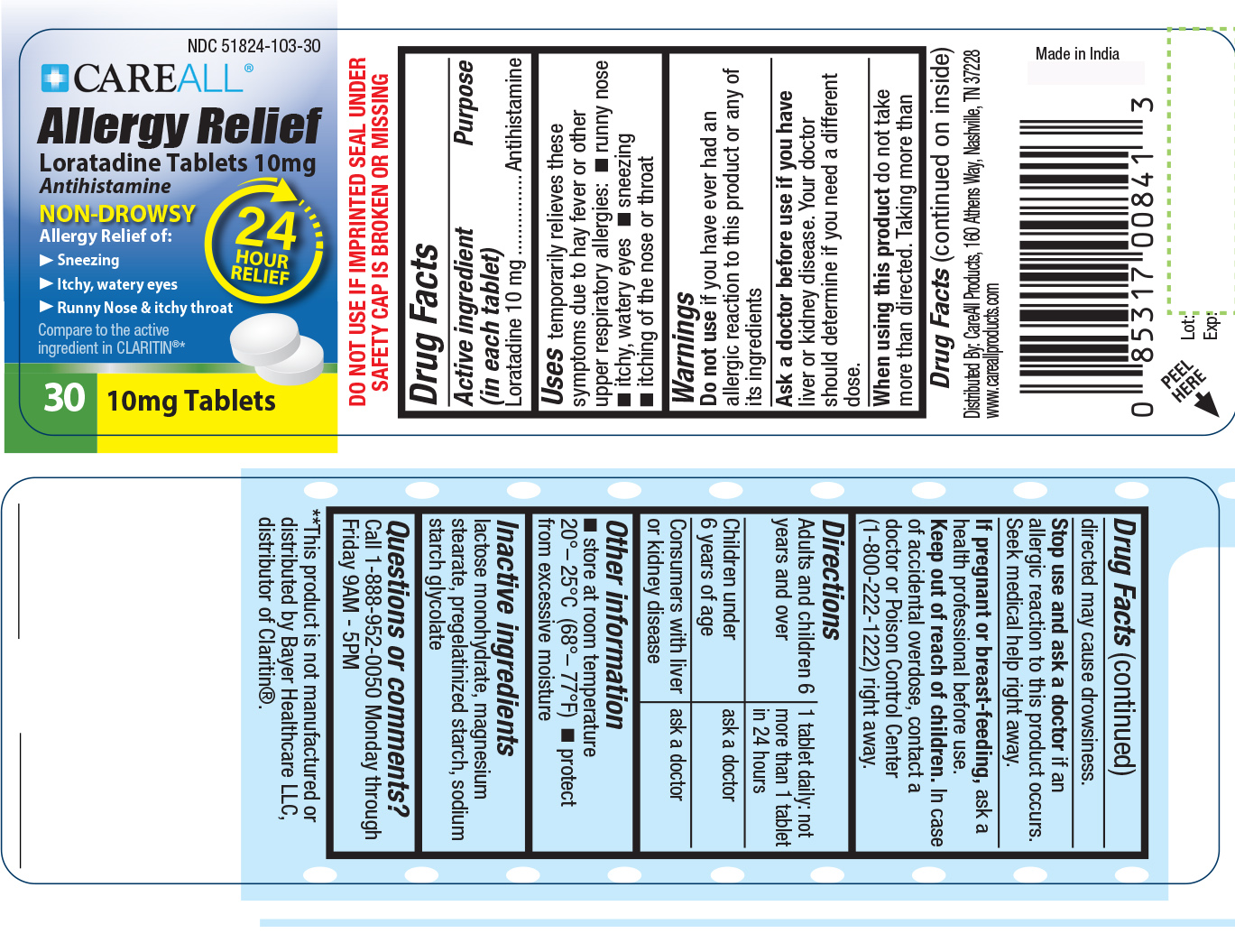 DRUG LABEL: CAREALL Allergy Relief
NDC: 51824-103 | Form: TABLET
Manufacturer: New World Imports
Category: otc | Type: HUMAN OTC DRUG LABEL
Date: 20251201

ACTIVE INGREDIENTS: LORATADINE 10 mg/1 1
INACTIVE INGREDIENTS: MAGNESIUM STEARATE; SODIUM STARCH GLYCOLATE TYPE A; LACTOSE MONOHYDRATE; STARCH, CORN

Drug Facts

ACTIVE INGREDIENT

Loratadine 10mg

PURPOSE

Antihistamine

KEEP OUT OF REACH OF CHILDREN

In case of accidental overdose, contact a doctor or Poison Control Center right away (1-800-222-1222)

INDICATIONS AND USAGE

Temporarily relieves these symptoms due to hay fever or other upper respiratory allergies:

runny nose, itchy/watery eyes, sneezing, itching of the nose or throat

WARNINGS

Do not useif you have ever had an allergic reaction to this product or any of its ingredients.

Ask a doctor before useif you have liver or kidney disease. Your doctor should determine if you need a different dose.

When using this productdo not take more than directed. Taking more than directed may cause drowsiness.

Stop use and ask a doctorif an allergic reaction to this product occurs. Seek medical help right away.

DOSAGE AND ADMINISTRATION

Adult and children over 6 years old:1 tablets daily: no more than 1 tablet in 24 hours.

Children under 6 years of age:ask a doctor

Consumers with liver or kidney disease: ask a doctor

INACTIVE INGREDIENT

lactose monohydrate, magnesium stearate, pregelatinized starch, sodium starch glycolate.

OTHER SAFETY INFORMATION

Store between 20-25 degrees celcius (68-77 degrees farhenheit).

Protect from excessive moisture

Do not use if imprinted seal under bottle cap is broken or missing

You may report side effects 1-888-952-0050